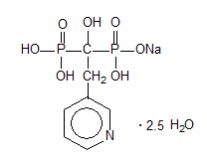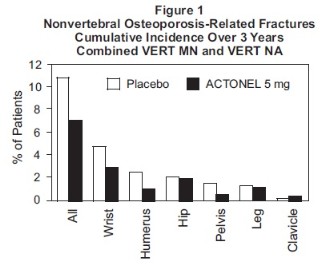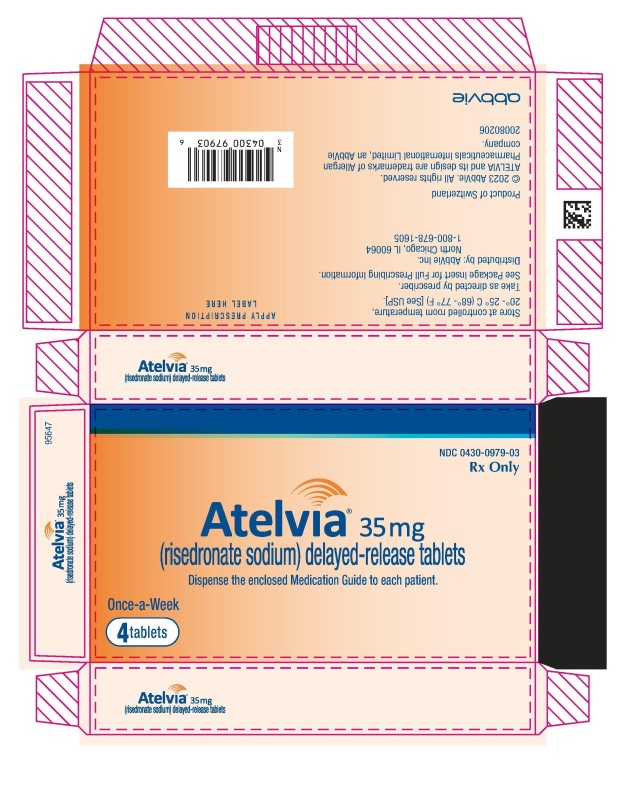 DRUG LABEL: Atelvia
NDC: 0430-0979 | Form: TABLET, DELAYED RELEASE
Manufacturer: Allergan, Inc.
Category: prescription | Type: HUMAN PRESCRIPTION DRUG LABEL
Date: 20260203

ACTIVE INGREDIENTS: RISEDRONATE SODIUM HEMIPENTAHYDRATE 30.1 mg/1 1; RISEDRONATE SODIUM MONOHYDRATE 4.9 mg/1 1
INACTIVE INGREDIENTS: EDETATE DISODIUM; FERRIC OXIDE YELLOW; MAGNESIUM STEARATE; METHACRYLIC ACID AND ETHYL ACRYLATE COPOLYMER; POLYSORBATE 80; CELLULOSE, MICROCRYSTALLINE; SILICON DIOXIDE; SODIUM STARCH GLYCOLATE TYPE A; STEARIC ACID; TALC; TRIETHYL CITRATE

HIGHLIGHTS OF PRESCRIBING INFORMATION

These highlights do not include all the information needed to use ATELVIA safely and effectively. See full prescribing information for ATELVIA.
ATELVIA® (risedronate sodium) delayed-release tablets
Initial U.S. Approval: 1998

RECENT MAJOR CHANGES

Warnings and Precautions, Atypical Fractures Including Femoral Fractures (5.6) ………………...………..…….…........................................... 02/2026

1 INDICATIONS AND USAGE

Atelvia is a bisphosphonate in a delayed-release formulation and is indicated for treatment of postmenopausal osteoporosis (1.1)

Limitations of Use

Optimal duration of use has not been determined. For patients at low-risk for fracture, consider drug discontinuation after 3 to 5 years of use (1.2)

2 DOSAGE AND ADMINISTRATION

One 35 mg delayed-release tablet once-a-week (2.1)

Instruct patients to:

- Take Atelvia in the morning immediately following breakfast with at least 4 ounces of plain water (2.2)
- Avoid lying down for 30 minutes after taking Atelvia (2.2)
- Take supplemental calcium and vitamin D if dietary intake is inadequate (2.3)

3 DOSAGE FORMS AND STRENGTHS

Delayed-release tablets: 35 mg (3)

4 CONTRAINDICATIONS

- Abnormalities of the esophagus which delay esophageal emptying such as stricture or achalasia (4, 5.2)
- Inability to stand or sit upright for at least 30 minutes (4, 5.2)
- Hypocalcemia (4, 5.3)
- Known hypersensitivity to any component of this product (4, 6.2)

5 WARNINGS AND PRECAUTIONS

- Products Containing Same Active Ingredient: Patients receiving Actonel should not be treated with Atelvia (5.1)
- Upper Gastrointestinal Adverse Reactions can occur. Instruct patients to follow dosing instructions. Discontinue use if new or worsening symptoms occur (5.2)
- Hypocalcemia may worsen and must be corrected prior to use (5.3)
- Osteonecrosis of the Jaw has been reported (5.4)
- Severe Bone, Joint, Muscle Pain may occur. Discontinue use if severe symptoms develop (5.5, 6.2)
- Atypical Fractures Including Femoral Fractures have been reported. Patients with new thigh or groin pain should be evaluated to rule out a femoral fracture. Risk/benefit of continuing bisphosphonate therapy should be re-evaluated in these patients and interruption of bisphosphonate therapy should be considered (5.6)

6 ADVERSE REACTIONS

Most common adverse reactions (greater than 5%) include: diarrhea, influenza, arthralgia, back pain, and abdominal pain (6.1)

Hypersensitivity reactions (angioedema, generalized rash, bullous skin reactions, Stevens-Johnson syndrome, and toxic epidermal necrolysis), and eye inflammation (iritis, uveitis) have been reported rarely (6.2)

To report SUSPECTED ADVERSE REACTIONS, contact AbbVie Inc at 1-800-633-9110 or FDA at 1-800-FDA-1088 or www.fda.gov/medwatch.

7 DRUG INTERACTIONS

Calcium supplements, antacids, proton pump inhibitors (PPIs), H2 blockers, magnesium-based supplements or laxatives, and iron preparations interfere with the absorption of Atelvia (7.1, 7.2)

8 USE IN SPECIFIC POPULATIONS

- Pregnancy: Discontinue when pregnancy is recognized (8.1)
- Atelvia is not recommended for use in patients with severe renal impairment (creatinine clearance less than 30 mL/min) (5.7, 8.6, 12.3)
- Atelvia is not indicated for use in pediatric patients (8.4)

FULL PRESCRIBING INFORMATION

1 INDICATIONS AND USAGE

1.1 Postmenopausal Osteoporosis

Atelvia is indicated for the treatment of osteoporosis in postmenopausal women. In postmenopausal women, risedronate sodium has been shown to reduce the incidence of vertebral fractures and a composite endpoint of nonvertebral osteoporosis-related fractures [see Clinical Studies (14.1)].

1.2 Important Limitations of Use

The optimal duration of use has not been determined. The safety and effectiveness of Atelvia for the treatment of osteoporosis are based on clinical data of one year duration. All patients on bisphosphonate therapy should have the need for continued therapy re-evaluated on a periodic basis. Patients at low-risk for fracture should be considered for drug discontinuation after 3 to 5 years of use. Patients who discontinue therapy should have their risk for fracture re-evaluated periodically.

2 DOSAGE AND ADMINISTRATION

2.1 Treatment of Postmenopausal Osteoporosis

[see Indications and Usage (1.1)]

The recommended regimen is:

- one 35 mg delayed-release tablet orally, taken once-a-week

2.2 Important Administration Instructions

Instruct patients to do the following:

- Take Atelvia in the morning immediately following breakfast. Atelvia should be taken immediately following breakfast and not under fasting conditions because of a higher risk of abdominal pain if taken before breakfast when fasting.
- Swallow Atelvia whole while in an upright position and with at least 4 ounces of plain water to facilitate delivery to the stomach. Avoid lying down for 30 minutes after taking the medication [see Warnings and Precautions (5.2)].
- Do not chew, cut, or crush Atelvia tablets.

2.3 Recommendations for Calcium and Vitamin D Supplementation

Instruct patients to take supplemental calcium and vitamin D if dietary intake is inadequate [see Warnings and Precautions (5.3)] and to take calcium supplements, antacids, magnesium-based supplements or laxatives, and iron preparations at a different time of the day as they interfere with the absorption of Atelvia.

2.4 Administration Instructions for Missed Doses

If the once-weekly dose is missed, instruct patients to take one tablet on the morning after they remember and return to taking one tablet once-a-week, as originally scheduled on their chosen day. Patients should not take two tablets on the same day.

3 DOSAGE FORMS AND STRENGTHS

Delayed-release tablets: 35 mg, yellow, oval-shaped, and engraved with EC 35 on one side.

4 CONTRAINDICATIONS

Atelvia is contraindicated in patients with the following conditions:

- Abnormalities of the esophagus which delay esophageal emptying such as stricture or achalasia [see Warnings and Precautions (5.2)]
- Inability to stand or sit upright for at least 30 minutes [see Dosage and Administration (2), Warnings and Precautions (5.2)]
- Hypocalcemia [see Warnings and Precautions (5.3)]
- Known hypersensitivity to any component of this product. Angioedema, generalized rash, bullous skin reactions, Stevens-Johnson syndrome and toxic epidermal necrolysis have been reported [see Adverse Reactions (6.2)]

5 WARNINGS AND PRECAUTIONS

5.1 Drug Products with the Same Active Ingredient

Atelvia contains the same active ingredient found in Actonel®. A patient being treated with Actonel should not receive Atelvia.

5.2 Upper Gastrointestinal Adverse Reactions

Atelvia, like other bisphosphonates administered orally, may cause local irritation of the upper gastrointestinal mucosa. Because of these possible irritant effects and a potential for worsening of the underlying disease, caution should be used when Atelvia is given to patients with active upper gastrointestinal problems (such as known Barrett’s esophagus, dysphagia, other esophageal diseases, gastritis, duodenitis or ulcers) [see Contraindications (4), Adverse Reactions (6.1), Information for Patients (17)].

Esophageal adverse experiences, such as esophagitis, esophageal ulcers and esophageal erosions, occasionally with bleeding and rarely followed by esophageal stricture or perforation, have been reported in patients receiving treatment with oral bisphosphonates. In some cases, these have been severe and required hospitalization. Physicians should therefore be alert to any signs or symptoms signaling a possible esophageal reaction and patients should be instructed to discontinue Atelvia and seek medical attention if they develop dysphagia, odynophagia, retrosternal pain or new or worsening heartburn.

The risk of severe esophageal adverse experiences appears to be greater in patients who lie down after taking oral bisphosphonates and/or who fail to swallow it with the recommended 4 ounces of water, and/or who continue to take oral bisphosphonates after developing symptoms suggestive of esophageal irritation. Therefore, it is very important that the full dosing instructions are provided to, and understood by, the patient [see Dosage and Administration (2)]. In patients who cannot comply with dosing instructions due to mental disability, therapy with Atelvia should be used under appropriate supervision.

There have been post-marketing reports of gastric and duodenal ulcers with oral bisphosphonate use, some severe and with complications, although no increased risk was observed in controlled clinical trials.

5.3 Mineral Metabolism

Hypocalcemia has been reported in patients taking Atelvia. Treat hypocalcemia and other disturbances of bone and mineral metabolism should be effectively treated before starting Atelvia therapy. Instruct patients to take supplemental calcium and vitamin D if their dietary intake is inadequate. Adequate intake of calcium and vitamin D is important in all patients [see Contraindications (4), Adverse Reactions (6.1), Information for Patients (17)].

5.4 Jaw Osteonecrosis

Osteonecrosis of the jaw (ONJ), which can occur spontaneously, is generally associated with tooth extraction and/or local infection with delayed healing, and has been reported in patients taking bisphosphonates, including risedronate. Known risk factors for osteonecrosis of the jaw include invasive dental procedures (for example, tooth extraction, dental implants, boney surgery), diagnosis of cancer, concomitant therapies (for example, chemotherapy, corticosteroids, angiogenesis inhibitors), poor oral hygiene, and co-morbid disorders (for example, periodontal and/or other pre-existing dental disease, anemia, coagulopathy, infection, ill-fitting dentures). The risk of ONJ may increase with duration of exposure to bisphosphonates.

For patients requiring invasive dental procedures, discontinuation of bisphosphonate treatment may reduce the risk for ONJ. Clinical judgment of the treating physician and/or oral surgeon should guide the management plan of each patient based on individual benefit/risk assessment.

Patients who develop ONJ while on bisphosphonate therapy should receive care by an oral surgeon. In these patients, extensive dental surgery to treat ONJ may exacerbate the condition. Discontinuation of bisphosphonate therapy should be considered based on individual benefit/risk assessment [see Adverse Reactions (6.2)].

5.5 Musculoskeletal Pain

In postmarketing experience, there have been reports of severe and occasionally incapacitating bone, joint, and/or muscle pain in patients taking bisphosphonates [see Adverse Reactions (6.2)]. The time to onset of symptoms varied from one day to several months after starting the drug. Most patients had relief of symptoms after stopping medication. A subset had recurrence of symptoms when rechallenged with the same drug or another bisphosphonate. Consider discontinuing use if severe symptoms develop.

5.6 Atypical Fractures Including Femoral Fractures

Atypical, low-energy, or low trauma fractures of the femoral shaft have been reported during treatment with bisphosphonates, including risedronate, in patients with osteoporosis. Atypical femur and other fractures most commonly occur with minimal or no trauma to the affected area. These fractures occurred anywhere in the femoral shaft from just below the lesser trochanter to above the supracondylar flare and are traverse or short oblique in orientation without evidence of comminution. Atypical fractures of other bones have also been reported. They may be bilateral. These fractures can also occur in osteoporotic patients who have not been treated with bisphosphonates. Concomitant treatment with glucocorticoids may also induce these fractures.

Prodromal pain in the affected area, usually presenting as dull, aching thigh pain, weeks to months before a complete fracture occurs was reported by patients.

Any patient with a history of bisphosphonate exposure who presents with thigh or groin pain should be suspected of having an atypical fracture and should be evaluated to rule out an incomplete femur fracture. Bony pain in other locations should also be considered for evaluation of atypical fracture. Patients presenting with an atypical fracture should also be assessed for symptoms and signs of fracture in the contralateral limb. Risk/benefit of continuing bisphosphonate therapy should be re-evaluated in these patients and interruption of bisphosphonate therapy should be considered.

5.7 Renal Impairment

Atelvia is not recommended for use in patients with severe renal impairment (creatinine clearance less than 30 mL/min) because of lack of clinical experience.

5.8 Laboratory Test Interactions

Bisphosphonates are known to interfere with the use of bone-imaging agents. Specific studies with Atelvia have not been performed.

6 ADVERSE REACTIONS

The following clinically significant adverse drug reactions are described elsewhere in the labeling:

- Drug Products with the Same Active Ingredient [see Warnings and Precautions (5.1)]
- Upper Gastrointestinal Adverse Reactions [see Warnings and Precautions (5.2)]
- Mineral Metabolism [see Warnings and Precautions (5.3)]
- Jaw Osteonecrosis [see Warnings and Precautions (5.4)]
- Musculoskeletal Pain [see Warnings and Precautions (5.5)]
- Atypical Fractures Including Femoral Fractures [see Warnings and Precautions (5.6)]
- Renal Impairment [see Warnings and Precautions (5.7)]
- Laboratory Test Interactions [see Warnings and Precautions (5.8)]

6.1 Clinical Studies Experience

Because clinical trials are conducted under widely varying conditions, adverse reaction rates observed in the clinical trials of a drug cannot be directly compared to rates in the clinical trials of another drug and may not reflect the rates observed in practice.

Treatment of Postmenopausal Osteoporosis

Once-a-Week Dosing with Atelvia (risedronate sodium) delayed-release tablets

The safety of Atelvia 35 mg once-a-week in the treatment of postmenopausal osteoporosis was assessed in a 1-year, double-blind, multicenter study comparing Atelvia 35 mg once-a-week to risedronate sodium immediate-release 5 mg daily in postmenopausal women 50 years of age or older. Atelvia was administered either at least 30 minutes before (N = 308) or immediately following (N = 307) breakfast, and risedronate sodium immediate-release 5 mg daily (N = 307) was administered at least 30 minutes before breakfast. Patients with pre-existing gastrointestinal disease and concomitant use of non-steroidal anti-inflammatory drugs, proton pump inhibitors, and H2 antagonists were included in this clinical trial. All women received daily supplementation with 1000 mg of elemental calcium plus 800 to 1000 international units vitamin D. As treatment with Atelvia resulted in a significantly higher incidence of abdominal pain when administered before breakfast under fasting conditions, safety results that follow refer only to Atelvia 35 mg once-a-week immediately following breakfast and risedronate sodium immediate-release 5 mg daily.

The incidence of all-cause mortality was 0.0% in the Atelvia 35 mg once-a-week group and 0.3% in the risedronate sodium immediate-release 5 mg daily group. The incidence of serious adverse reactions was 6.5% in the Atelvia 35 mg once-a-week group and 7.2% in the risedronate sodium immediate-release 5 mg daily group. The percentage of patients who withdrew from the study due to adverse reactions was 9.1% in the Atelvia 35 mg once-a-week group and 8.1% in the risedronate sodium immediate-release 5 mg daily group. The overall safety and tolerability profiles of the two dosing regimens were similar. Table 1 lists adverse reactions reported in greater than or equal to 2% of patients. Adverse reactions are shown without attribution of causality.

Table 1 Adverse Reactions Occurring at a Frequency of greater than or equal to 2% in Either Treatment Group
 | 35 mg Atelvia | 5 mg Risedronate sodium Immediate- release
 | Weekly | Daily
System Organ Class | N = 307 | N = 307
Preferred Term | % | %
Gastrointestinal disorders
Diarrhea | 8.8 | 4.9
Abdominal pain | 5.2 | 2.9
Constipation | 4.9 | 2.9
Vomiting | 4.9 | 1.6
Dyspepsia | 3.9 | 3.9
Nausea | 3.6 | 3.9
Abdominal pain upper | 2.9 | 2.3
Infections and infestations
Influenza | 7.2 | 6.2
Bronchitis | 3.9 | 4.2
Upper respiratory tract infection | 3.6 | 2.6
Musculoskeletal and connective tissue disorders
Arthralgia | 6.8 | 7.8
Back pain | 6.8 | 5.9
Pain in extremity | 3.9 | 2.3
Musculoskeletal pain | 2.0 | 1.6
Muscle spasms | 1.0 | 2.3
Nervous system disorders
Dizziness | 2.6 | 3.3
Headache | 2.6 | 4.9

Acute Phase Reactions: Symptoms consistent with acute phase reaction have been reported with bisphosphonate use. The overall incidence of acute phase reaction was 2.3% in the Atelvia 35 mg once-a-week group and 1.3% in the risedronate sodium immediate-release 5 mg daily group. These incidence rates are based on reporting of one or more pre-specified acute phase reaction-like symptoms within 3 days of the first dose and for a duration of 7 days or less.

Gastrointestinal Adverse Reactions: Adverse reactions related to the upper gastrointestinal tract occurred in 16% of subjects treated with Atelvia 35 mg once-a-week and 15% of subjects treated with risedronate sodium immediate-release 5 mg daily. The incidence of upper gastrointestinal tract adverse reactions in the Atelvia 35 mg once-a-week and risedronate sodium immediate-release 5 mg daily groups were: abdominal pain (5.2% versus 2.9%), dyspepsia (3.9% versus 3.9%), upper abdominal pain (2.9% versus 2.3%), gastritis (1.0% versus 1.0%), and gastroesophageal reflux disease (1.0% versus 1.6%). Study discontinuation due to abdominal pain occurred in 1.3% of the Atelvia 35 mg once-a-week group and 0.7% of the risedronate sodium immediate-release 5 mg daily group.

Musculoskeletal Adverse Reactions: Selected musculoskeletal adverse reactions were reported in 16% of subjects treated with Atelvia 35 mg once-a-week and 15% of subjects treated with risedronate sodium immediate-release 5 mg daily. The incidence of musculoskeletal adverse reactions in the Atelvia 35 mg once-a-week and risedronate sodium immediate-release 5 mg daily groups were: arthralgia (6.8% versus 7.8%), back pain (6.8% versus 5.9%), musculoskeletal pain (2.0% versus 1.6%), and myalgia (1.3% versus 1.0%).

Laboratory Test Findings:

Parathyroid hormone: The effect of Atelvia 35 mg once-a-week and risedronate sodium immediate-release 5 mg daily on parathyroid hormone was evaluated in postmenopausal women with osteoporosis. At week 52, in subjects with normal levels at baseline, PTH levels greater than 65 pg/mL (upper limit of normal) were noted in 9% of subjects receiving Atelvia 35 mg once-a-week and 8% of subjects receiving risedronate sodium immediate-release 5 mg daily. In subjects with normal levels at baseline, PTH levels greater than 97 pg/mL (1.5 times the upper limit of normal) were seen in 2% of subjects receiving Atelvia 35 mg once-a-week and no subjects receiving risedronate sodium immediate-release 5 mg daily. There were no clinically significant differences between treatment groups for levels of calcium, phosphorus and magnesium.

Daily Dosing with risedronate sodium immediate-release 5 mg tablets

The safety of risedronate sodium immediate-release 5 mg once daily in the treatment of postmenopausal osteoporosis was assessed in four randomized, double-blind, placebo-controlled multinational trials of 3232 women aged 38 to 85 years with postmenopausal osteoporosis. The duration of the trials was up to three years, with 1619 patients exposed to placebo and 1613 patients exposed to risedronate sodium immediate-release 5 mg daily. Patients with pre-existing gastrointestinal disease and concomitant use of non-steroidal anti-inflammatory drugs, proton pump inhibitors (PPIs), and H2 antagonists were included in these clinical trials. All women received 1000 mg of elemental calcium plus vitamin D supplementation up to 500 international units per day if their 25-hydroxyvitamin D3 level was below normal at baseline.

The incidence of all-cause mortality was 2.0% in the placebo group and 1.7% in the risedronate sodium immediate-release 5 mg daily group. The incidence of serious adverse reactions was 24.6% in the placebo group and 27.2% in the risedronate sodium immediate-release 5 mg daily group. The percentage of patients who withdrew from the study due to adverse reactions was 15.6% in the placebo group and 14.8% in the risedronate sodium immediate-release 5 mg daily group. The most common adverse reactions reported in greater than 10% of subjects were: back pain, arthralgia, abdominal pain and dyspepsia.

Gastrointestinal Adverse Reactions: The incidence of adverse reactions in the placebo and risedronate sodium immediate-release 5 mg daily groups were: abdominal pain (9.9% versus 12.2%), diarrhea (10.0% versus 10.8%), dyspepsia (10.6% versus 10.8%), and gastritis (2.3% versus 2.7%). Duodenitis and glossitis have been reported uncommonly in the risedronate sodium immediate-release 5 mg daily group (0.1% to 1%). In patients with active upper gastrointestinal disease at baseline, the incidence of upper gastrointestinal adverse reactions was similar between the placebo and risedronate sodium immediate-release 5 mg daily groups.

Musculoskeletal Adverse Reactions: The incidence of adverse reactions in the placebo and risedronate sodium immediate-release 5 mg daily groups were: back pain (26.1% versus 28.0%), arthralgia (22.1% versus 23.7%), myalgia (6.2% versus 6.7%), and bone pain (4.8% versus 5.3%).

Laboratory Test Findings: Throughout the Phase 3 studies, transient decreases from baseline in serum calcium (less than 1%) and serum phosphate (less than 3%) and compensatory increases in serum PTH levels (less than 30%) were observed within 6 months in patients in osteoporosis clinical trials treated with risedronate sodium immediate-release 5 mg daily. There were no significant differences in serum calcium, phosphate, or PTH levels between placebo and risedronate sodium immediate-release 5 mg daily at 3 years. Serum calcium levels below 8 mg/dL were observed in 18 patients, 9 (0.5%) in each treatment arm (placebo and risedronate sodium immediate-release 5 mg daily). Serum phosphorus levels below 2 mg/dL were observed in 14 patients, 3 (0.2%) treated with placebo and 11 (0.6%) treated with risedronate sodium immediate-release 5 mg daily. There have been rare reports (less than 0.1%) of abnormal liver function tests.

Endoscopic Findings: In the risedronate sodium immediate-release 5 mg daily clinical trials, endoscopic evaluation was encouraged in any patient with moderate-to-severe gastrointestinal complaints, while maintaining the blind. Endoscopies were performed on equal numbers of patients between the placebo and treated groups [75 (14.5%) placebo; 75 (11.9%) risedronate sodium immediate-release 5 mg daily]. Clinically important findings (perforations, ulcers, or bleeding) among this symptomatic population were similar between groups (51% placebo; 39% risedronate sodium immediate-release 5 mg daily).

6.2 Postmarketing Experience

The following adverse reactions have been reported with the use of Atelvia or bisphosphonate products. Because these adverse reactions are reported voluntarily from a population of uncertain size, it is not always possible to reliably estimate their frequency or establish a causal relationship to drug exposure.

Hypersensitivity Reactions

Hypersensitivity and skin reactions have been reported, including angioedema, generalized rash, bullous skin reactions, Stevens-Johnson syndrome and toxic epidermal necrolysis.

Gastrointestinal Adverse Reactions

Reactions involving upper gastrointestinal irritation, such as esophagitis and esophageal or gastric ulcers, have been reported [see Warnings and Precautions (5.2)].

Musculoskeletal

Bone, joint, or muscle pain, described as severe or incapacitating, have been reported rarely [see Warnings and Precautions (5.5)]; low-energy femoral shaft and subtrochanteric fractures, and atypical fractures of other bones [see Warnings and Precautions (5.6)].

Eye Inflammation

Reactions of eye inflammation including iritis and uveitis have been reported rarely.

Jaw Osteonecrosis

Osteonecrosis of the jaw has been reported rarely [see Warnings and Precautions (5.4)].

Pulmonary

Asthma exacerbations

7 DRUG INTERACTIONS

Risedronate is not metabolized and does not induce or inhibit hepatic microsomal drug-metabolizing enzymes (for example, Cytochrome P450).

7.1 Calcium Supplements/Antacids

When Atelvia was administered following breakfast, the co-administration of a tablet containing 600 mg of elemental calcium and 400 international units vitamin D reduced risedronate bioavailability by approximately 38% [see Clinical Pharmacology (12.3)]. Calcium supplements, antacids, magnesium-based supplements or laxatives, and iron preparations interfere with the absorption of Atelvia and should not be taken together.

7.2 Histamine 2 (H 2) Blockers and Proton Pump Inhibitors (PPIs)

Drugs that raise stomach pH (for example, PPIs or H2 blockers) may cause faster drug release from enteric coated (delayed-release) drug products such as Atelvia. Co-administration of Atelvia with the PPI, esomeprazole, increased risedronate bioavailability. The maximum plasma concentration (Cmax) and the area under the plasma concentration (AUC) were increased by 60 percent and 22 percent, respectively.

Concomitant administration of Atelvia and H2 blockers or PPIs is not recommended.

7.3 Hormone Therapy

Concomitant use of Atelvia with estrogens and estrogen agonist/antagonists has not been studied.

7.4 Aspirin/Nonsteroidal Anti-Inflammatory Drugs

In the Phase 3 study comparing Atelvia 35 mg once-a-week immediately following breakfast and risedronate sodium 5 mg daily, 18% of NSAID users (any use) in both groups developed upper gastrointestinal adverse reactions. Among non-users, 13% of patients taking Atelvia 35 mg once-a-week immediately following breakfast developed upper gastrointestinal adverse reactions, compared to 12% taking risedronate sodium 5 mg daily.

8 USE IN SPECIFIC POPULATIONS

8.1 Pregnancy

Risk Summary

Available data on use of Atelvia in pregnant women are insufficient to inform drug-associated risk of adverse maternal or fetal outcomes. Discontinue Atelvia when pregnancy is recognized.

In animal reproduction studies, daily oral administration of risedronate to pregnant rats during organogenesis decreased neonatal survival and body weight at doses approximately 5 and 26 times, respectively, the highest recommended human daily dose of 30 mg (based on body surface area, mg/m^2), the dose indicated for treatment of Paget’s disease. A low incidence of cleft palate was observed in fetuses of dams treated at doses approximately equal to the 30 mg human daily dose. Delayed skeletal ossification was observed in fetuses of dams treated at approximately 2.5 to 5 times the 30 mg human daily dose. Periparturient mortality due to maternal hypocalcemia occurred in dams and neonates upon daily oral administration of risedronate to pregnant rats during mating and/or gestation starting at doses equivalent to the 30 mg daily human dose.

Bisphosphonates are incorporated into the bone matrix, from which they are gradually released over a period of weeks to years. The amount of bisphosphonate incorporated into adult bone available for release into the systemic circulation is directly related to the dose and duration of bisphosphonate use. Consequently, based on mechanism of action of bisphosphonates, there is a potential risk of fetal harm, predominantly skeletal, if a woman becomes pregnant after completing a course of bisphosphonate therapy. The impact of variables such as time between cessation of bisphosphonate therapy to conception, the particular bisphosphonate used, and the route of administration (intravenous versus oral) on this risk has not been studied.

The estimated background risk of major birth defects and miscarriage for the indicated populations is unknown. All pregnancies have a background risk of birth defects, loss, or other adverse outcomes. In the U.S. general population, the estimated background risks of major birth defects and miscarriage in clinically recognized pregnancies is 2-4% and 15-20%, respectively.

Data

Animal data

In animal studies, pregnant rats received risedronate sodium during organogenesis at doses 1 to 26 times the human Paget’s disease dose of 30 mg/day (based on body surface area, mg/m^2). Survival of neonates was decreased in rats treated during gestation with oral doses approximately 5 times the human dose and body weight was decreased in neonates from dams treated with approximately 26 times the human dose. A low incidence of cleft palate was observed in fetuses from female rats treated with oral doses approximately equal to the human dose. The number of fetuses exhibiting incomplete ossification of sternebrae or skull of dams treated with approximately 2.5 times the human dose was significantly increased compared to controls. Both incomplete ossification and unossified sternebrae were increased in fetuses of dams treated with oral doses approximately 5 times the human dose.

No significant ossification effects were seen in fetuses of rabbits treated with oral doses approximately 7 times the human dose (the highest dose tested). However, 1 of 14 litters were aborted and 1 of 14 litters were delivered prematurely.

Periparturient mortality due to maternal hypocalcemia occurred in dams and neonates when pregnant rats were treated daily during mating and/or gestation with oral doses equivalent to the human dose or higher.

8.2 Lactation

Risk Summary

There are no data to assess the presence of risedronate in human milk, the effects on the breastfed infant, or the effects on milk production. A small degree of lacteal transfer occurred in nursing rats. The concentration of the drug in animal milk does not necessarily predict the concentration of drug in human milk. However, when a drug is present in animal milk, it is likely that the drug will be present in human milk. The developmental and health benefits of breast-feeding should be considered along with the mother’s clinical need for Atelvia and any potential adverse effects on the breast-fed child from Atelvia or from the underlying maternal condition.

Data

Animal Data

Risedronate was detected in neonates of lactating rats given a single oral dose of risedronate at 24-hours post-dosing, indicating a small degree of lacteal transfer.

8.3 Females and Males of Reproductive Potential

Infertility

There are no data available in humans. Female and male fertility may be impaired based on animal studies demonstrating adverse effects of Atelvia on fertility parameters [see Nonclinical Toxicology (13.1)].

8.4 Pediatric Use

Atelvia is not indicated for use in pediatric patients.

The safety and effectiveness of risedronate sodium immediate-release was assessed in a one-year, randomized, double-blind, placebo-controlled study of 143 pediatric patients (94 received risedronate) with osteogenesis imperfecta (OI). The enrolled population was predominantly patients with mild OI (85% Type-I), aged 4 to less than 16 years, 50% male and 82% Caucasian, with a mean lumbar spine BMD Z-score of -2.08 (2.08 standard deviations below the mean for age-matched controls). Patients received either a 2.5 mg (less than or equal to 30 kg body weight) or 5 mg (greater than 30 kg body weight) daily oral dose. After one year, an increase in lumbar spine BMD in the risedronate sodium immediate-release group compared to the placebo group was observed. However, treatment with risedronate sodium immediate-release did not result in a reduction in the risk of fracture in pediatric patients with OI. In risedronate sodium immediate-release treated subjects, no mineralization defects were noted in paired bone biopsy specimens obtained at baseline and month 12.

The overall safety profile of risedronate in OI patients treated for up to 12 months was generally similar to that of adults with osteoporosis. However, there was an increased incidence of vomiting compared to placebo. In this study, vomiting was observed in 15% of children treated with risedronate sodium immediate-release and 6% of patients treated with placebo. Other adverse reactions reported in greater than or equal to 10% of patients treated with risedronate sodium immediate-release and with a higher frequency than placebo were: pain in the extremity (21% with risedronate sodium immediate-release versus 16% with placebo), headache (20% versus 8%), back pain (17% versus 10%), pain (15% versus 10%), upper abdominal pain (11% versus 8%), and bone pain (10% versus 4%).

8.5 Geriatric Use

Of the patients receiving Atelvia in postmenopausal osteoporosis studies, 59% were 65 and over, while 13% were 75 and over. No overall differences in safety or effectiveness were observed between these patients and younger patients, and other reported clinical experience has not identified differences in responses between the elderly and younger patients, but greater sensitivity of some older individuals cannot be ruled out.

8.6 Renal Impairment

Atelvia is not recommended for use in patients with severe renal impairment (creatinine clearance less than 30 mL/min) because of lack of clinical experience. No dosage adjustment is necessary in patients with a creatinine clearance greater than or equal to 30 mL/min.

8.7 Hepatic Impairment

No studies have been performed to assess risedronate sodium’s safety or efficacy in patients with hepatic impairment. Risedronate is not metabolized in human liver preparations. Dosage adjustment is unlikely to be needed in patients with hepatic impairment.

10 OVERDOSAGE

Decreases in serum calcium and phosphorus following substantial overdose may be expected in some patients. Signs and symptoms of hypocalcemia may also occur in some of these patients. While milk or antacids containing calcium may be given to bind risedronate sodium immediate- release and reduce absorption of the drug, the impact of this intervention for Atelvia delayed-release tablets has not been evaluated.

In cases of substantial overdose, gastric lavage may be considered to remove unabsorbed drug. Standard procedures that are effective for treating hypocalcemia, including the administration of calcium intravenously, would be expected to restore physiologic amounts of ionized calcium and to relieve signs and symptoms of hypocalcemia.

Lethality after single oral doses of risedronate was seen in female rats at 903 mg/kg and male rats at 1703 mg/kg. The minimum lethal dose in mice and rabbits was 4000 mg/kg and 1000 mg/kg, respectively. These values represent 320 to 620 times the human Paget’s disease dose of 30 mg/day based on surface area (mg/m^2).

11 DESCRIPTION

Atelvia (risedronate sodium) delayed-release tablets contain a pH-sensitive enteric coating and a chelating agent (EDTA).

Risedronate is a pyridinyl bisphosphonate that inhibits osteoclast-mediated bone resorption and modulates bone metabolism. Each Atelvia tablet for oral administration contains the equivalent of 35 mg of anhydrous risedronate sodium in the form of the hemi-pentahydrate with small amounts of monohydrate. The empirical formula for risedronate sodium hemi-pentahydrate is C7H10NO7P2Na •2.5 H2O. The chemical name of risedronate sodium is [1-hydroxy-2-(3-pyridinyl)ethylidene]bis[phosphonic acid] monosodium salt. The chemical structure of risedronate sodium hemi-pentahydrate is the following:

Molecular Weight:

Anhydrous: 305.10

Hemi-pentahydrate: 350.13

Risedronate sodium is a fine, white to off-white, odorless, crystalline powder. It is soluble in water and in aqueous solutions, and essentially insoluble in common organic solvents.

Inactive Ingredients

Edetate disodium, ferric oxide yellow, magnesium stearate, methacrylic acid copolymer, polysorbate 80, silicified microcrystalline cellulose (ProSolv SMCC90), simethicone, sodium starch glycolate, stearic acid, talc, and triethyl citrate.

12 CLINICAL PHARMACOLOGY

12.1 Mechanism of Action

Risedronate has an affinity for hydroxyapatite crystals in bone and acts as an antiresorptive agent. At the cellular level, risedronate inhibits osteoclasts. The osteoclasts adhere normally to the bone surface, but show evidence of reduced active resorption (for example, lack of ruffled border). Histomorphometry in rats, dogs, and minipigs showed that risedronate treatment reduces bone turnover (activation frequency, that is, the rate at which bone remodeling sites are activated) and bone resorption at remodeling sites.

12.2 Pharmacodynamics

Risedronate treatment decreases the elevated rate of bone turnover that is typically seen in postmenopausal osteoporosis. In clinical trials, administration of risedronate sodium immediate- release to postmenopausal women resulted in decreases in biochemical markers of bone turnover, including urinary deoxypyridinoline/creatinine and urinary collagen cross-linked N-telopeptide (markers of bone resorption) and serum bone-specific alkaline phosphatase (a marker of bone formation). At the 5 mg daily dose, decreases in deoxypyridinoline/creatinine were evident within 14 days of treatment. Changes in bone formation markers were observed later than changes in resorption markers, as expected, due to the coupled nature of bone resorption and bone formation; decreases in bone-specific alkaline phosphatase of about 20% were evident within 3 months of treatment. Bone turnover markers reached a nadir of about 40% below baseline values by the sixth month of treatment and remained stable with continued treatment for up to 3 years. Bone turnover is decreased as early as 14 days and maximally within about 6 months of treatment, with achievement of a new steady-state that more nearly approximates the rate of bone turnover seen in premenopausal women. In a 1-year study comparing Atelvia 35 mg weekly taken immediately after breakfast versus risedronate sodium immediate-release 5 mg daily oral dosing regimens in postmenopausal women, mean decreases from baseline at 1 year in urinary collagen cross-linked N-telopeptide were 47% in the Atelvia 35 mg once-a-week following breakfast group and 42% in the risedronate sodium immediate-release 5 mg daily group. In addition, serum bone-specific alkaline phosphatase at 1 year was reduced by 33% in the Atelvia 35 mg once-a-week following breakfast group and 32% in the risedronate sodium immediate-release 5 mg daily group.

12.3 Pharmacokinetics

Absorption

The mean absolute oral bioavailability of the 30 mg risedronate sodium immediate-release tablet taken 4 hours prior to a meal is 0.63% (90% confidence interval [CI]: 0.54% to 0.75%) and is similar to an oral solution. The time to peak concentration (Tmax) for Atelvia tablet is approximately 3 hours when administered in the morning 4 hours prior to a meal.

Food Effect

In a crossover pharmacokinetic study, the bioavailability of Atelvia 35 mg delayed-release tablets decreased by approximately 30% when administered immediately after a high-fat breakfast compared to administration in the morning 4 hours before a meal.

The bioavailability of the 35 mg Atelvia tablet administered after a high-fat breakfast was similar to risedronate sodium 35 mg immediate-release tablet dosed 4 hours before a meal in one study and was approximately 2- to 4-fold greater than the immediate-release 35 mg tablet administered 30 minutes prior to a high-fat breakfast.

In a separate study, Atelvia administered after dinner exhibited approximately 87% increase in risedronate exposure compared to administration following a breakfast. The safety and efficacy of dosing Atelvia after dinner has not been evaluated [see Dosage and Administration (2)].

Distribution

The mean steady-state volume of distribution for risedronate is 13.8 L/kg in humans. Human plasma protein binding of drug is about 24%. Preclinical studies in rats and dogs dosed intravenously with single doses of [^14C] risedronate indicate that approximately 60% of the dose is distributed to bone. The remainder of the dose is excreted in the urine. After multiple oral dosing in rats, the uptake of risedronate in soft tissues was in the range of 0.001% to 0.01%.

Metabolism

There is no evidence of systemic metabolism of risedronate.

Excretion

In young healthy subjects, approximately half of the absorbed dose of risedronate was excreted in urine within 24 hours, and 85% of an intravenous dose was recovered in the urine over 28 days. Based on simultaneous modeling of serum and urine data for the risedronate sodium immediate-release tablets, mean renal clearance was 105 mL/min (CV = 34%) and mean total clearance was 122 mL/min (CV = 19%), with the difference primarily reflecting nonrenal clearance or clearance due to adsorption to bone. The renal clearance is not concentration dependent, and there is a linear relationship between renal clearance and creatinine clearance. Unabsorbed drug is eliminated unchanged in feces. In osteopenic postmenopausal women, the terminal exponential half-life was 561 hours, mean renal clearance was 52 mL/min (CV = 25%), and mean total clearance was 73 mL/min (CV = 15%).

Specific Populations

Pediatric: Atelvia is not indicated for use in pediatric patients [see Pediatric Use (8.4)].

Geriatric: Effect of age on bioavailability of Atelvia has not been evaluated. Based on data from risedronate immediate-release tablet, bioavailability and disposition of risedronate are similar in elderly (greater than 60 years of age) and younger subjects. No dosage adjustment is necessary.

Race: Pharmacokinetic differences due to race have not been studied. The clinical trial of Atelvia was conducted mostly in Caucasians.

Renal Impairment: Risedronate is excreted unchanged primarily via the kidney. As compared to persons with normal renal function, the renal clearance of risedronate was decreased by about 70% in patients with creatinine clearance of approximately 30 mL/min. Atelvia is not recommended for use in patients with severe renal impairment (creatinine clearance less than 30 mL/min). No dosage adjustment is necessary in patients with a creatinine clearance greater than or equal to 30 mL/min.

Hepatic Impairment: No studies have been performed to assess risedronate’s safety or efficacy in patients with hepatic impairment. Risedronate is not metabolized in rat, dog, and human liver preparations. Insignificant amounts (less than 0.1% of intravenous dose) of drug are excreted in the bile in rats. Therefore, dosage adjustment is unlikely to be needed in patients with hepatic impairment.

Drug Interactions: Risedronate is not metabolized and does not induce or inhibit hepatic microsomal drug-metabolizing enzymes (for example, Cytochrome P450).

Calcium supplement: A Phase 1 single-dose, cross-over study in 101 postmenopausal women evaluated the relative bioavailability of Atelvia 35 mg delayed-release tablets taken after breakfast and following a 600 mg elemental calcium/400 international units vitamin D supplement, compared to Atelvia alone taken after breakfast without calcium or vitamin D supplementation. The addition of the calcium/vitamin D supplement following the meal resulted in an approximate 38% reduction in the amount of risedronate absorbed [see Drug Interactions (7)].

Proton Pump Inhibitors: A Phase 1, 2-period, cross-over study in 60 healthy postmenopausal female subjects evaluated the relative bioavailability of a single dose Atelvia 35 mg delayed-release tablet taken after breakfast following 6 days of esomeprazole magnesium delayed release 40 mg capsules. On Day 6, esomeprazole 40 mg capsule was administered with 240 mL water one hour before breakfast and Atelvia 35 mg tablet was administered with 240 mL water within 10 minutes after a standard breakfast. The Cmax and AUCinf of risedronate were increased by 60 percent and 22 percent, respectively, in presence of esomeprazole.

13 NONCLINICAL TOXICOLOGY

13.1 Carcinogenesis, Mutagenesis, Impairment of Fertility

Carcinogenesis

In a 104-week carcinogenicity study, rats were administered daily oral doses up to approximately 8 times the human Paget’s disease dose of 30 mg/day. There were no significant drug-induced tumor findings in male or female rats. The high dose male group was terminated early in the study (Week 93) due to excessive toxicity, and data from this group were not included in the statistical evaluation of the study results. In an 80-week carcinogenicity study, mice were administered daily oral doses approximately 6.5 times the human dose. There were no significant drug-induced tumor findings in male or female mice.

Mutagenesis

Risedronate did not exhibit genetic toxicity in the following assays: In vitro bacterial mutagenesis in Salmonella and E. coli (Ames assay), mammalian cell mutagenesis in CHO/HGPRT assay, unscheduled DNA synthesis in rat hepatocytes and an assessment of chromosomal aberrations in vivo in rat bone marrow. Risedronate was positive in a chromosomal aberration assay in CHO cells at highly cytotoxic concentrations (greater than 675 mcg/mL, survival of 6% to 7%). When the assay was repeated at doses exhibiting appropriate cell survival (29%), there was no evidence of chromosomal damage.

Impairment of Fertility

In female rats, ovulation was inhibited at an oral dose approximately 5 times the human dose. Decreased implantation was noted in female rats treated with doses approximately 2.5 times the human dose. In male rats, testicular and epididymal atrophy and inflammation were noted at approximately 13 times the human dose. Testicular atrophy was also noted in male rats after 13 weeks of treatment at oral doses approximately 5 times the human dose. There was moderate-to-severe spermatid maturation block after 13 weeks in male dogs at an oral dose approximately 8 times the human dose. These findings tended to increase in severity with increased dose and exposure time.

Dosing multiples provided above are based on the recommended human Paget’s disease dose of 30 mg/day and normalized using body surface area (mg/m^2). Actual doses were 24 mg/kg/day in rats, 32 mg/kg/day in mice, and 8, 16 and 40 mg/kg/day in dogs.

13.2 Animal Toxicology and/or Pharmacology

Risedronate demonstrated potent anti-osteoclast, antiresorptive activity in ovariectomized rats and minipigs. Bone mass and biomechanical strength were increased dose-dependently at daily oral doses up to 4 and 25 times the recommended human dose of 5 mg/day for rats and minipigs, respectively. Risedronate treatment maintained the positive correlation between BMD and bone strength and did not have a negative effect on bone structure or mineralization. In intact dogs, risedronate induced positive bone balance at the level of the bone remodeling unit at oral doses ranging from 0.5 to 1.5 times the human dose of 5 mg/day.

In dogs treated with an oral dose approximately 5 times the human dose of 5 mg/day, risedronate caused a delay in fracture healing of the radius. The observed delay in fracture healing is similar to other bisphosphonates. This effect did not occur at a dose approximately 0.5 times the human daily dose.

The Schenk rat assay, based on histologic examination of the epiphyses of growing rats after drug treatment, demonstrated that risedronate did not interfere with bone mineralization even at the highest dose tested, which was approximately 3500 times the lowest antiresorptive dose in this model (1.5 mcg/kg/day) and approximately 800 times the human dose of 5 mg/day. This indicates that Atelvia administered at the therapeutic dose is unlikely to induce osteomalacia.

Dosing multiples provided above are based on the recommended human osteoporosis dose of 5 mg/day and normalized using body surface area (mg/m^2).

14 CLINICAL STUDIES

14.1 Treatment of Osteoporosis in Postmenopausal Women

The efficacy of Atelvia 35 mg once-a-week in the treatment of postmenopausal osteoporosis was demonstrated in a randomized, double-blind, active-control trial of approximately 900 subjects. All patients in this study received supplemental calcium (1000 mg/day) and vitamin D (800 to 1000 international units/day). The primary efficacy endpoint was percent change in lumbar spine bone mineral density at 1 year.

Atelvia 35 mg once-a-week administered after breakfast was shown to be non-inferior to risedronate sodium immediate-release 5 mg daily. Table 2 presents the primary efficacy analysis, percent change in lumbar spine BMD, in the intent-to-treat population with last observation carried forward (LOCF).

Table 2 Lumbar Spine BMD - Percent Change from Baseline at Endpoint[a]
 | Risedronate sodium immediate-release 5 mg Daily | Atelvia 35 mg Once-a-Week Following Breakfast
 | N = 307 | N = 307
Primary Efficacy (LOCF)
n | 270 | 261
LS Mean (95% CI) | 3.1* (2.7, 3.5) | 3.3* (2.9, 3.7)
LS Mean Difference[b] (95% CI) |  | -0.2 (-0.8, 0.3)
N = number of intent-to-treat patients within specified treatment; n = number of patients with values at the visit.
*Indicates a statistically significant difference from baseline determined from 95% CI unadjusted for multiple comparisons.
LS = Least Squares
[a] at 1 year LOCF
[b] LS Mean Difference is 5 mg daily minus 35 mg weekly treatment.

Fracture efficacy with risedronate sodium immediate-release 5 mg daily

The fracture efficacy of risedronate sodium immediate-release 5 mg daily in the treatment of postmenopausal osteoporosis was demonstrated in 2 large, randomized, placebo-controlled, double-blind studies that enrolled a total of almost 4000 postmenopausal women under similar protocols. The Multinational study (VERT MN) (risedronate sodium immediate-release 5 mg daily, N = 408) was conducted primarily in Europe and Australia; a second study was conducted in North America (VERT NA) (risedronate sodium immediate-release 5 mg daily, N = 821). Patients were selected on the basis of radiographic evidence of previous vertebral fracture, and therefore, had established disease. The average number of prevalent vertebral fractures per patient at study entry was 4 in VERT MN, and 2.5 in VERT NA, with a broad range of baseline BMD levels. All patients in these studies received supplemental calcium 1000 mg/day. Patients with low 25-hydroxyvitamin D3 levels (approximately 40 nmol/L or less) also received 500 international units/day supplemental vitamin D.

Effect on Vertebral Fractures

Fractures of previously undeformed vertebrae (new fractures) and worsening of pre-existing vertebral fractures were diagnosed radiographically; some of these fractures were also associated with symptoms (that is, clinical fractures). Spinal radiographs were scheduled annually and prospectively planned analyses were based on the time to a patient’s first diagnosed fracture. The primary endpoint for these studies was the incidence of new and worsening vertebral fractures across the period of 0 to 3 years. Risedronate sodium immediate-release 5 mg daily significantly reduced the incidence of new and worsening vertebral fractures and of new vertebral fractures in both VERT NA and VERT MN at all time points (Table 3). The reduction in risk seen in the subgroup of patients who had 2 or more vertebral fractures at study entry was similar to that seen in the overall study population.

Table 3 The Effect of Risedronate sodium 5 mg Immediate-Release Daily on the Risk of Vertebral Fractures
 | Proportion of Patients with Fracture (%)a
VERT NA | Placebo N = 678 | Risedronate sodium 5 mg N = 696 | Absolute Risk Reduction (%) | Relative Risk Reduction (%)
New and Worsening
0 to 1 Year | 7.2 | 3.9 | 3.3 | 49
0 to 2 Years | 12.8 | 8.0 | 4.8 | 42
0 to 3 Years | 18.5 | 13.9 | 4.6 | 33
New
0 to 1 Year | 6.4 | 2.4 | 4.0 | 65
0 to 2 Years | 11.7 | 5.8 | 5.9 | 55
0 to 3 Years | 16.3 | 11.3 | 5.0 | 41
VERT MN | Placebo N = 346 | Risedronate sodium 5 mg N = 344 | Absolute Risk Reduction (%) | Relative Risk Reduction (%)
New and Worsening
0 to 1 Year | 15.3 | 8.2 | 7.1 | 50
0 to 2 Years | 28.3 | 13.9 | 14.4 | 56
0 to 3 Years | 34.0 | 21.8 | 12.2 | 46
New
0 to 1 Year | 13.3 | 5.6 | 7.7 | 61
0 to 2 Years | 24.7 | 11.6 | 13.1 | 59
0 to 3 Years | 29.0 | 18.1 | 10.9 | 49
aCalculated by Kaplan-Meier methodology.

Effect on Osteoporosis-Related Nonvertebral Fractures

In VERT MN and VERT NA, a prospectively planned efficacy endpoint was defined consisting of all radiographically confirmed fractures of skeletal sites accepted as associated with osteoporosis. Fractures at these sites were collectively referred to as osteoporosis-related nonvertebral fractures. Risedronate sodium immediate-release 5 mg daily significantly reduced the incidence of nonvertebral osteoporosis-related fractures over 3 years in VERT NA (8% versus 5%; relative risk reduction 39%) and reduced the fracture incidence in VERT MN from 16% to 11%. There was a significant reduction from 11% to 7% when the studies were combined, with a corresponding 36% reduction in relative risk. Figure 1 shows the overall results as well as the results at the individual skeletal sites for the combined studies.

Histology/Histomorphometry

Bone biopsies from 110 postmenopausal women were obtained at endpoint in the VERT NA study. Patients had received placebo or daily risedronate sodium immediate-release (2.5 mg or 5 mg) for 2 to 3 years. Histologic evaluation (N = 103) showed no osteomalacia, impaired bone mineralization, or other adverse effects on bone in risedronate sodium immediate-release treated women. These findings demonstrate that bone formed during risedronate sodium immediate-release administration is of normal quality. The histomorphometric parameter mineralizing surface, an index of bone turnover, was assessed based upon baseline and post-treatment biopsy samples from 21 treated with placebo and 23 patients treated with risedronate sodium immediate-release 5 mg daily. Mineralizing surface decreased moderately in risedronate sodium immediate-release treated patients (median percent change: placebo, -21%; risedronate sodium immediate-release 5 mg daily, -74%), consistent with the known effects of treatment on bone turnover.

Effect on Height

In the two 3-year osteoporosis treatment studies, standing height was measured yearly by stadiometer. Both risedronate sodium immediate-release 5 mg daily and placebo-treated groups lost height during the studies. Patients who received risedronate sodium immediate-release 5 mg daily had a statistically significantly smaller loss of height than those who received placebo. In VERT MN, the median annual height change was -2.4 mm/yr in the placebo group compared to -1.3 mm/yr in the risedronate sodium immediate-release 5 mg daily group. In VERT NA, the median annual height change was -1.1 mm/yr in the placebo group compared to -0.7 mm/yr in the risedronate sodium immediate-release 5 mg daily group.

Effect on Bone Mineral Density

The results of 4 randomized, placebo-controlled trials in women with postmenopausal osteoporosis (VERT MN, VERT NA, BMD MN, BMD NA) demonstrate that risedronate sodium immediate-release 5 mg daily increases BMD at the spine, hip, and wrist compared to the effects seen with placebo. Table 4 displays the significant increases in BMD seen at the lumbar spine, femoral neck, femoral trochanter, and midshaft radius in these trials compared to placebo. In both VERT studies (VERT MN and VERT NA), risedronate sodium immediate-release 5 mg daily produced increases in lumbar spine BMD that were progressive over the 3 years of treatment, and were statistically significant relative to baseline and to placebo at 6 months and at all later time points.

Table 4 Mean Percent Increase in BMD from Baseline in Patients Taking Risedronate sodium Immediate-Release 5 mg or Placebo at Endpointa
 | VERT MNb |  | VERT NAb |  | BMD MNc |  | BMD NAc
 | Placebo N = 323 | 5 mg N = 323 | Placebo N = 599 | 5 mg N = 606 | Placebo N = 161 | 5 mg N = 148 | Placebo N = 191 | 5 mg N = 193
Lumbar Spine | 1.0 | 6.6 | 0.8 | 5.0 | 0.0 | 4.0 | 0.2 | 4.8
Femoral Neck | -1.4 | 1.6 | -1.0 | 1.4 | -1.1 | 1.3 | 0.1 | 2.4
Femoral Trochanter | -1.9 | 3.9 | -0.5 | 3.0 | -0.6 | 2.5 | 1.3 | 4.0
Midshaft Radius | -1.5* | 0.2* | -1.2* | 0.1* | ND |  | ND
aThe endpoint value is the value at the study's last time point for all patients who had BMD measured at that time; otherwise the last post-baseline BMD value prior to the study's last time point is used.
bThe duration of the studies was 3 years.
cThe duration of the studies was 1.5 to 2 years.
*BMD of the midshaft radius was measured in a subset of centers in VERT MN (placebo, N = 222;
5 mg, N = 214) and VERT NA (placebo, N = 310; 5 mg, N = 306).
ND = analysis not done

16 HOW SUPPLIED/STORAGE AND HANDLING

Atelvia® (risedronate sodium) delayed-release tablets are:

35 mg, yellow, oval-shaped, and engraved with EC 35 on one side.

NDC 0430-0979-03 Dosepak of 4 tablets

Store at controlled room temperature 20° to 25° C (68° to 77° F) [see USP].

17 PATIENT COUNSELING INFORMATION

See FDA-approved patient labeling (Medication Guide)

Instruct patients to read the Medication Guide before starting therapy with Atelvia and to re-read it each time the prescription is renewed.

Instruct patients that Atelvia and Actonel contain the same active ingredient and if they are taking Actonel, they should not take Atelvia [see Warnings and Precautions (5.1)].

Instruct patients to pay particular attention to the dosing instructions as clinical benefits may be compromised by failure to take the drug according to instructions.

Instruct patients to take Atelvia in the morning, while in an upright position (sitting or standing) with at least 4 ounces of plain water immediately following breakfast. Atelvia should not be taken before breakfast.

Instruct patients to swallow Atelvia tablets whole. Patients should not chew, cut, or crush the tablet because of a potential for oropharyngeal irritation, and because the tablet coating is an important part of the delayed-release formulation. Patients should not lie down for 30 minutes after taking the medication.

Instruct patients that if they develop symptoms of esophageal disease (such as difficulty or pain upon swallowing, retrosternal pain or severe persistent or worsening heartburn) they should consult their physician before continuing Atelvia [see Warnings and Precautions (5.2)].

If a dose of Atelvia 35 mg once-a-week is missed, instruct the patient to take one tablet on the morning after they remember and return to taking one tablet once-a-week, as originally scheduled on their chosen day. Patients should not take 2 tablets on the same day.

Instruct patients to take supplemental calcium and vitamin D if dietary intake is inadequate [see Warnings and Precautions (5.3)].

Instruct patients to take calcium supplements, antacids, magnesium-based supplements or laxatives, and iron preparations at a different time of the day because they interfere with the absorption of Atelvia.

Remind patients to give all of their healthcare providers an accurate medication history. Instruct patients to tell all of their healthcare providers that they are taking Atelvia. Patients should be instructed that any time they have a medical problem they think may be from Atelvia they should talk to their doctor.

Distributed by:
AbbVie Inc.
North Chicago, IL 60064

For all medical inquiries contact:
AbbVie Medical Communications
1-800-633-9110

© 2026 AbbVie. All rights reserved.
Atelvia and its design are trademarks of Allergan Pharmaceuticals International Limited, an AbbVie company.

Content Updated: February 2026

133189 R-1

Medication Guide
Atelvia® (uh-TEL-v-uh)
(risedronate sodium)
delayed-release tablets

Read this Medication Guide that comes with Atelvia® before you start taking it and each time you get a refill. There may be new information. This Medication Guide does not take the place of talking with your doctor about your medical condition or your treatment. Talk to your doctor if you have any questions about Atelvia, there may be new information about it.

What is the most important information I should know about Atelvia?

Atelvia can cause serious side effects including:

1. Esophagus problems
2. Low calcium levels in your blood (hypocalcemia)
3. Severe jaw bone problems (osteonecrosis)
4. Bone, joint, or muscle pain
5. Unusual breaks in thigh and other bones

1. Esophagus problems.

Some people who take Atelvia may develop problems in the esophagus (the tube that connects the mouth and the stomach). These problems include irritation, inflammation, or ulcers of the esophagus which may sometimes bleed.

- It is important that you take Atelvia exactly as prescribed to help lower your chance of getting esophagus problems. (See the section “How should I take Atelvia?”)
- Stop taking Atelvia and call your doctor right away if you get chest pain, new or worsening heartburn, or have trouble or pain when you swallow.

2. Low calcium levels in your blood (hypocalcemia).

Atelvia may lower the calcium levels in your blood. If you have low blood calcium before you start taking Atelvia, it may get worse during treatment. Your low blood calcium must be treated before you take Atelvia. Most people with low blood calcium levels do not have symptoms, but some people may have symptoms. Call your doctor right away if you have symptoms of low blood calcium such as:

- Spasms, twitches, or cramps in your muscles
- Numbness or tingling in your fingers, toes, or around your mouth

Your doctor may prescribe calcium and vitamin D to help prevent low calcium levels in your blood, while you are taking Atelvia. Take calcium and vitamin D as your doctor tells you to.

3. Severe jaw bone problems (osteonecrosis).

Severe jaw bone problems may happen when you take Atelvia. Your doctor should examine your mouth before you start Atelvia. Your doctor may tell you to see your dentist before you start Atelvia. It is important for you to practice good mouth care during treatment with Atelvia.

4. Bone, joint, or muscle pain.

Some people who take Atelvia develop severe bone, joint, or muscle pain.

5. Unusual breaks in thigh and other bones.

Some people have had unusual bone breaks, including the thigh bone, when taking Atelvia. A break in the thigh bone can feel like a new pain in your hip, groin, or thigh. People taking Atelvia can also have breaks in other bones.

Call your doctor right away if you have any of these side effects.

What is Atelvia?

Atelvia is a prescription medicine used to treat osteoporosis in women after menopause.

It is not known how long Atelvia works for the treatment and prevention of osteoporosis. You should see your doctor regularly to determine if Atelvia is still right for you.

Atelvia is not for use in children.

Who should not take Atelvia?

Do not take Atelvia if you:

- Have certain problems with your esophagus, the tube that connects your mouth and stomach
- Cannot sit or stand up for at least 30 minutes
- Have low blood calcium (hypocalcemia)
- Are allergic to any of the other ingredients in Atelvia. See the end of this leaflet for a complete list of ingredients in Atelvia.

What should I tell my healthcare provider before taking Atelvia?

Before you take Atelvia, tell your healthcare provider if you:

- Have problems swallowing
- Have stomach or digestive problems
- Have low blood calcium
- Plan to have dental surgery or teeth removed
- Have kidney problems
- Have been told you have trouble absorbing mineral in your stomach or intestines (malabsorption syndrome)
- Are pregnant, plan to become pregnant, or suspect that you are pregnant. If you become pregnant while taking Atelvia, stop taking it and contact your doctor. It is not known if Atelvia can harm your unborn baby.
- Are breastfeeding or plan to breastfeed. It is not known if Atelvia passes into your breast milk and may harm your baby. You and your doctor should decide if you will take Atelvia or breastfeed. You should not do both.

Tell your doctor about all the medicines you take, including prescription and non-prescription medicines, vitamins and herbal supplements. Certain medicines may affect how Atelvia works.

Especially tell your doctor if you take:

- Actonel® or other medicines to treat osteoporosis
- calcium supplements
- antacids
- laxatives
- iron supplements

Ask your doctor or pharmacist for a list of these medications, if you are not sure.

Know the medicines you take. Keep a list of them to show your doctor and pharmacist when you get a new medicine.

How should I take Atelvia?

- Take Atelvia exactly as your doctor tells you.
- Take Atelvia 1 time a week right after breakfast. Choose a day of the week to take Atelvia that best fits your schedule.
- Take Atelvia with at least 4 ounces (about 1-half cup) of plain water.
- Swallow Atelvia tablets whole. Do not chew, cut, or crush Atelvia tablets before swallowing. If you cannot swallow Atelvia tablets whole, tell your doctor. You may need a different medicine.

After swallowing Atelvia wait at least 30 minutes:

- Before you lie down. You may sit, stand or walk, and do normal activities like reading.
- Before you take other medicines, including antacids, calcium, and other supplements and vitamins.

Do not lie down for at least 30 minutes after you take Atelvia.

If you miss your weekly Atelvia dose, take Atelvia the morning after you remember then return to your normal schedule. Do not take 2 doses at the same time.

You should take calcium and vitamin D as directed by your doctor.

If you take too much Atelvia, call your doctor. Do not try to vomit. Do not lie down.

What are the possible side effects of Atelvia?

Atelvia may cause serious side effects:

- See “What is the most important information I should know about Atelvia”.

The most common side effects of Atelvia include:

- diarrhea
- flu-like symptoms
- muscle pain
- back and joint pain
- upset stomach
- stomach area (abdominal) pain

You may get allergic reactions, such as hives, swelling of your face, lips, tongue, or throat.

Tell your doctor if you have any side effect that bothers you or that does not go away.

These are not all the possible side effects of Atelvia. For more information, ask your doctor or pharmacist.

Call your doctor for medical advice about side effects. You may report side effects to FDA at 1-800-FDA-1088.

How should I store Atelvia?

- Store Atelvia between 68° F to 77° F (20° C to 25° C).

Keep Atelvia and all medicines out of the reach of children.

General information about the safe and effective use of Atelvia

Medicines are sometimes prescribed for purposes other than those listed in a Patient Information Leaflet. Do not use Atelvia for a condition for which it was not prescribed. Do not give Atelvia to other people, even if they have the same symptoms you have. It may harm them.

This Medication Guide summarizes the most important information about Atelvia. If you would like more information, talk with your doctor. You can ask your pharmacist or doctor for information about Atelvia that is written for health professionals.

For more information, go to www.Atelvia.com or call 1-800-633-9110.

What are the ingredients in Atelvia?

Active ingredient: risedronate sodium

Inactive ingredients: Edetate disodium, ferric oxide yellow, magnesium stearate, methacrylic acid copolymer, polysorbate 80, silicified microcrystalline cellulose (ProSolv SMCC90), simethicone, sodium starch glycolate, stearic acid, talc, and triethyl citrate.

This Medication Guide has been approved by the U.S. Food and Drug Administration.

Distributed by:
AbbVie Inc.
North Chicago, IL 60064

For all medical inquiries contact:
AbbVie Medical Communications
1-800-633-9110

© 2026 AbbVie. All rights reserved.

Atelvia and its design are trademarks of Allergan Pharmaceuticals International Limited, an AbbVie company.

Content Updated: February 2026

133189 R-1

PACKAGE LABEL

PRINCIPAL DISPLAY PANEL

NDC 0430-0979-03
Rx Only
Atelvia® 35 mg
(risedronate sodium) delayed-release tablets
Dispense the enclosed Medication Guide to each patient
Once-a-Week
4 tablets